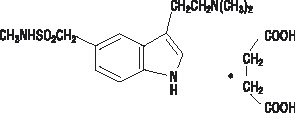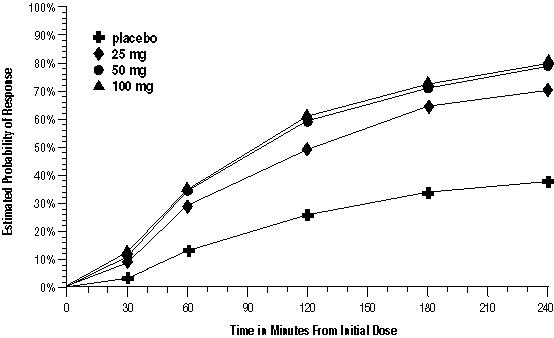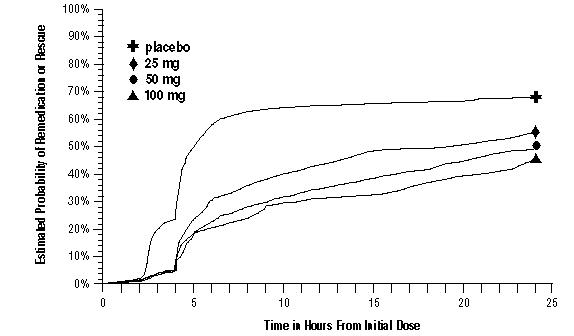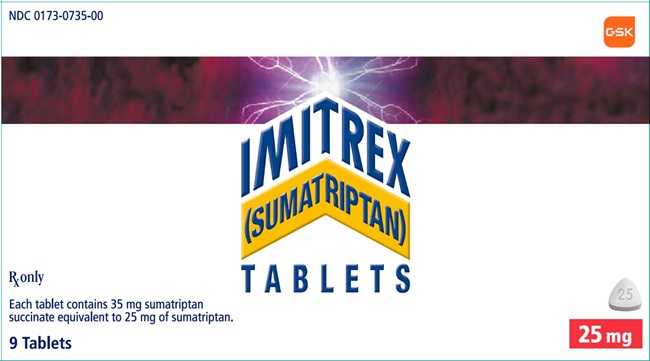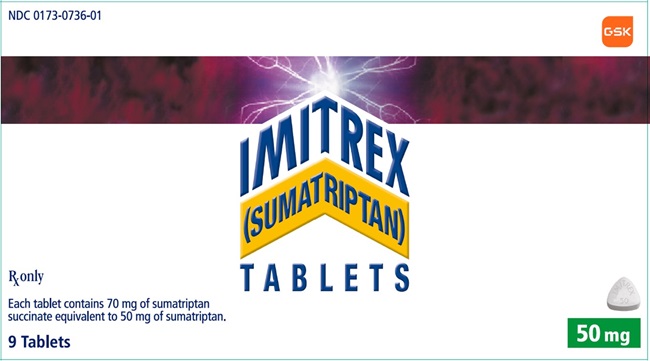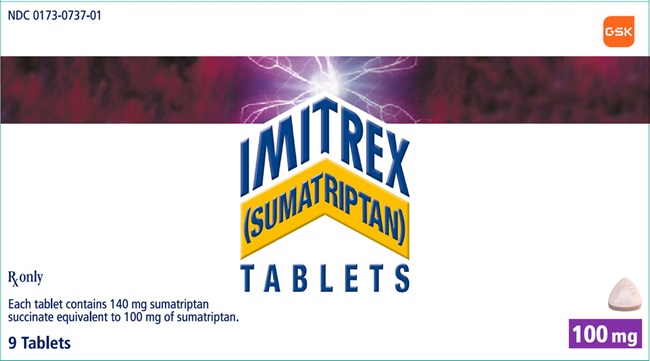 DRUG LABEL: IMITREX
NDC: 0173-0735 | Form: TABLET, FILM COATED
Manufacturer: GlaxoSmithKline LLC
Category: prescription | Type: HUMAN PRESCRIPTION DRUG LABEL
Date: 20251209

ACTIVE INGREDIENTS: SUMATRIPTAN SUCCINATE 25 mg/1 1
INACTIVE INGREDIENTS: CROSCARMELLOSE SODIUM; ANHYDROUS DIBASIC CALCIUM PHOSPHATE; MAGNESIUM STEARATE; MICROCRYSTALLINE CELLULOSE; SODIUM BICARBONATE

HIGHLIGHTS OF PRESCRIBING INFORMATION

These highlights do not include all the information needed to use IMITREX safely and effectively. See full prescribing information for IMITREX.
IMITREX (sumatriptan) tablets, for oral use
Initial U.S. Approval: 1992

1 INDICATIONS AND USAGE

IMITREX is a serotonin (5-HT1B/1D) receptor agonist (triptan) indicated for acute treatment of migraine with or without aura in adults. (1)

Limitations of Use:

- Use only if a clear diagnosis of migraine headache has been established. (1)
- Not indicated for the prophylactic therapy of migraine attacks. (1)
- Not indicated for the treatment of cluster headache. (1)

2 DOSAGE AND ADMINISTRATION

- Single dose of 25-mg, 50-mg, or 100-mg tablet. (2.1)
- A second dose should only be considered if some response to the first dose was observed. Separate doses by at least 2 hours. (2.1)
- Maximum dose in a 24-hour period: 200 mg. (2.1)
- Maximum single dose should not exceed 50 mg in patients with mild to moderate hepatic impairment. (2.2)

3 DOSAGE FORMS AND STRENGTHS

Tablets: 25 mg, 50 mg, and 100 mg (3)

4 CONTRAINDICATIONS

- History of coronary artery disease or coronary artery vasospasm (4)
- Wolff-Parkinson-White syndrome or other cardiac accessory conduction pathway disorders (4)
- History of stroke, transient ischemic attack, or hemiplegic or basilar migraine (4)
- Peripheral vascular disease (4)
- Ischemic bowel disease (4)
- Uncontrolled hypertension (4)
- Recent (within 24 hours) use of another 5-HT1 agonist (e.g., another triptan) or of an ergotamine-containing medication (4)
- Concurrent or recent (past 2 weeks) use of monoamine oxidase-A inhibitor (4)
- Hypersensitivity to IMITREX (angioedema and anaphylaxis seen) (4)
- Severe hepatic impairment (4)

5 WARNINGS AND PRECAUTIONS

- Myocardial ischemia/infarction and Prinzmetal’s angina: Perform cardiac evaluation in patients with multiple cardiovascular risk factors. (5.1)
- Arrhythmias: Discontinue IMITREX if occurs. (5.2)
- Chest/throat/neck/jaw pain, tightness, pressure, or heaviness: Generally not associated with myocardial ischemia; evaluate for coronary artery disease in patients at high risk. (5.3)
- Cerebral hemorrhage, subarachnoid hemorrhage, and stroke: Discontinue IMITREX if occurs. (5.4)
- Gastrointestinal ischemic reactions and peripheral vasospastic reactions: Discontinue IMITREX if occurs. (5.5)
- Medication overuse headache: Detoxification may be necessary. (5.6)
- Serotonin syndrome: Discontinue IMITREX if occurs. (5.7)
- Seizures: Use with caution in patients with epilepsy or a lowered seizure threshold. (5.10)

6 ADVERSE REACTIONS

Most common adverse reactions (≥2% and >placebo) were paresthesia, warm/cold sensation, chest pain/tightness/pressure and/or heaviness, neck/throat/jaw pain/tightness/pressure, other sensations of pain/pressure/tightness/heaviness, vertigo, and malaise/fatigue. (6.1)

To report SUSPECTED ADVERSE REACTIONS, contact GlaxoSmithKline at 1-888-825-5249 or FDA at 1-800-FDA-1088 or www.fda.gov/medwatch.

8 USE IN SPECIFIC POPULATIONS

Pregnancy: Based on animal data, may cause fetal harm. (8.1)

FULL PRESCRIBING INFORMATION

1 INDICATIONS AND USAGE

IMITREX tablets are indicated for the acute treatment of migraine with or without aura in adults.

Limitations of Use:

- Use only if a clear diagnosis of migraine headache has been established. If a patient has no response to the first migraine attack treated with IMITREX, reconsider the diagnosis of migraine before IMITREX is administered to treat any subsequent attacks.
- IMITREX is not indicated for the prevention of migraine attacks.
- Safety and effectiveness of IMITREX tablets have not been established for cluster headache.

2 DOSAGE AND ADMINISTRATION

2.1 Dosing Information

The recommended dose of IMITREX tablets is 25 mg, 50 mg, or 100 mg. Doses of 50 mg and 100 mg may provide a greater effect than the 25-mg dose, but doses of 100 mg may not provide a greater effect than the 50-mg dose. Higher doses may have a greater risk of adverse reactions [see Clinical Studies (14)].

If the migraine has not resolved by 2 hours after taking IMITREX tablets, or returns after a transient improvement, a second dose may be administered at least 2 hours after the first dose. The maximum daily dose is 200 mg in a 24-hour period.

Use after IMITREX Injection

If the migraine returns following an initial treatment with IMITREX (sumatriptan) injection, additional single IMITREX tablets (up to 100 mg/day) may be given with an interval of at least 2 hours between tablet doses.

The safety of treating an average of more than 4 headaches in a 30-day period has not been established.

2.2 Dosing in Patients with Hepatic Impairment

If treatment is deemed advisable in the presence of mild to moderate hepatic impairment, the maximum single dose should not exceed 50 mg [see Use in Specific Populations (8.6), Clinical Pharmacology (12.3)].

3 DOSAGE FORMS AND STRENGTHS

25-mg Tablets: White, triangular-shaped, film-coated, and debossed with “I” on one side and “25” on the other. Each tablet contains 35 mg of sumatriptan succinate equivalent to 25 mg of sumatriptan.

50-mg Tablets: White, triangular-shaped, film-coated, and debossed with “IMITREX 50” on one side and a chevron shape (^) on the other. Each tablet contains 70 mg of sumatriptan succinate equivalent to 50 mg of sumatriptan.

100-mg Tablets: Pink, triangular-shaped, film-coated, and debossed with “IMITREX 100” on one side and a chevron shape (^) on the other. Each tablet contains 140 mg of sumatriptan succinate equivalent to 100 mg of sumatriptan.

4 CONTRAINDICATIONS

IMITREX Tablets are contraindicated in patients with:

- Ischemic coronary artery disease (CAD) (angina pectoris, history of myocardial infarction, or documented silent ischemia) or coronary artery vasospasm, including Prinzmetal’s angina [see Warnings and Precautions (5.1)]
- Wolff-Parkinson-White syndrome or arrhythmias associated with other cardiac accessory conduction pathway disorders [see Warnings and Precautions (5.2)]
- History of stroke or transient ischemic attack (TIA) or history of hemiplegic or basilar migraine because these patients are at a higher risk of stroke [see Warnings and Precautions (5.4)]
- Peripheral vascular disease [see Warnings and Precautions (5.5)]
- Ischemic bowel disease [see Warnings and Precautions (5.5)]
- Uncontrolled hypertension [see Warnings and Precautions (5.8)]
- Recent use (i.e., within 24 hours) of ergotamine-containing medication, ergot-type medication (such as dihydroergotamine or methysergide), or another 5-hydroxytryptamine1 (5-HT1) agonist [see Drug Interactions (7.1, 7.3)]
- Concurrent administration of a monoamine oxidase (MAO)-A inhibitor or recent (within 2 weeks) use of an MAO-A inhibitor [see Drug Interactions (7.2), Clinical Pharmacology (12.3)]
- Hypersensitivity to IMITREX (angioedema and anaphylaxis seen) [see Warnings and Precautions (5.9)]
- Severe hepatic impairment [see Use in Specific Populations (8.6), Clinical Pharmacology (12.3)]

5 WARNINGS AND PRECAUTIONS

5.1 Myocardial Ischemia, Myocardial Infarction, and Prinzmetal’s Angina

The use of IMITREX tablets is contraindicated in patients with ischemic or vasospastic CAD. There have been rare reports of serious cardiac adverse reactions, including acute myocardial infarction, occurring within a few hours following administration of IMITREX tablets. Some of these reactions occurred in patients without known CAD. IMITREX tablets may cause coronary artery vasospasm (Prinzmetal’s angina), even in patients without a history of CAD.

Perform a cardiovascular evaluation in triptan-naive patients who have multiple cardiovascular risk factors (e.g., increased age, diabetes, hypertension, smoking, obesity, strong family history of CAD) prior to receiving IMITREX tablets. If there is evidence of CAD or coronary artery vasospasm, IMITREX tablets are contraindicated. For patients with multiple cardiovascular risk factors who have a negative cardiovascular evaluation, consider administering the first dose of IMITREX tablets in a medically supervised setting and performing an electrocardiogram (ECG) immediately following administration of IMITREX tablets. For such patients, consider periodic cardiovascular evaluation in intermittent long-term users of IMITREX tablets.

5.2 Arrhythmias

Life-threatening disturbances of cardiac rhythm, including ventricular tachycardia and ventricular fibrillation leading to death, have been reported within a few hours following the administration of 5-HT1 agonists. Discontinue IMITREX tablets if these disturbances occur. IMITREX tablets are contraindicated in patients with Wolff-Parkinson-White syndrome or arrhythmias associated with other cardiac accessory conduction pathway disorders.

5.3 Chest, Throat, Neck, and/or Jaw Pain/Tightness/Pressure

Sensations of tightness, pain, pressure, and heaviness in the precordium, throat, neck, and jaw commonly occur after treatment with IMITREX tablets and are usually non-cardiac in origin. However, perform a cardiac evaluation if these patients are at high cardiac risk. The use of IMITREX tablets is contraindicated in patients with CAD and those with Prinzmetal’s variant angina.

5.4 Cerebrovascular Events

Cerebral hemorrhage, subarachnoid hemorrhage, and stroke have occurred in patients treated with 5-HT1 agonists, and some have resulted in fatalities. In a number of cases, it appears possible that the cerebrovascular events were primary, the 5-HT1 agonist having been administered in the incorrect belief that the symptoms experienced were a consequence of migraine when they were not. Also, patients with migraine may be at increased risk of certain cerebrovascular events (e.g., stroke, hemorrhage, TIA). Discontinue IMITREX tablets if a cerebrovascular event occurs.

Before treating headaches in patients not previously diagnosed as migraineurs, and in migraineurs who present with atypical symptoms, exclude other potentially serious neurological conditions. IMITREX tablets are contraindicated in patients with a history of stroke or TIA.

5.5 Other Vasospasm Reactions

IMITREX tablets may cause non-coronary vasospastic reactions, such as peripheral vascular ischemia, gastrointestinal vascular ischemia and infarction (presenting with abdominal pain and bloody diarrhea), splenic infarction, and Raynaud’s syndrome. In patients who experience symptoms or signs suggestive of non-coronary vasospasm reaction following the use of any 5-HT1 agonist, rule out a vasospastic reaction before receiving additional IMITREX tablets.

Reports of transient and permanent blindness and significant partial vision loss have been reported with the use of 5‑HT1 agonists. Since visual disorders may be part of a migraine attack, a causal relationship between these events and the use of 5-HT1 agonists has not been clearly established.

5.6 Medication Overuse Headache

Overuse of acute migraine drugs (e.g., ergotamine, triptans, opioids, or combination of these drugs for 10 or more days per month) may lead to exacerbation of headache (medication overuse headache). Medication overuse headache may present as migraine-like daily headaches or as a marked increase in frequency of migraine attacks. Detoxification of patients, including withdrawal of the overused drugs, and treatment of withdrawal symptoms (which often includes a transient worsening of headache) may be necessary.

5.7 Serotonin Syndrome

Serotonin syndrome may occur with IMITREX tablets, particularly during coadministration with selective serotonin reuptake inhibitors (SSRIs), serotonin norepinephrine reuptake inhibitors (SNRIs), tricyclic antidepressants (TCAs), and MAO inhibitors [see Drug Interactions (7.4)]. Serotonin syndrome symptoms may include mental status changes (e.g., agitation, hallucinations, coma), autonomic instability (e.g., tachycardia, labile blood pressure, hyperthermia), neuromuscular aberrations (e.g., hyperreflexia, incoordination), and/or gastrointestinal symptoms (e.g., nausea, vomiting, diarrhea). The onset of symptoms usually occurs within minutes to hours of receiving a new or a greater dose of a serotonergic medication. Discontinue IMITREX tablets if serotonin syndrome is suspected.

5.8 Increase in Blood Pressure

Significant elevation in blood pressure, including hypertensive crisis with acute impairment of organ systems, has been reported on rare occasions in patients treated with 5-HT1 agonists, including patients without a history of hypertension. Monitor blood pressure in patients treated with IMITREX. IMITREX tablets are contraindicated in patients with uncontrolled hypertension.

5.9 Anaphylactic/Anaphylactoid Reactions

Anaphylactic/anaphylactoid reactions have occurred in patients receiving IMITREX. Such reactions can be life-threatening or fatal. In general, anaphylactic reactions to drugs are more likely to occur in individuals with a history of sensitivity to multiple allergens. IMITREX tablets are contraindicated in patients with a history of hypersensitivity reaction to IMITREX.

5.10 Seizures

Seizures have been reported following administration of IMITREX. Some have occurred in patients with either a history of seizures or concurrent conditions predisposing to seizures. There are also reports in patients where no such predisposing factors are apparent. IMITREX tablets should be used with caution in patients with a history of epilepsy or conditions associated with a lowered seizure threshold.

6 ADVERSE REACTIONS

The following adverse reactions are discussed in more detail in other sections of the prescribing information:

- Myocardial ischemia, myocardial infarction, and Prinzmetal’s angina [see Warnings and Precautions (5.1)]
- Arrhythmias [see Warnings and Precautions (5.2)]
- Chest, throat, neck, and/or jaw pain/tightness/pressure [see Warnings and Precautions (5.3)]
- Cerebrovascular events [see Warnings and Precautions (5.4)]
- Other vasospasm reactions [see Warnings and Precautions (5.5)]
- Medication overuse headache [see Warnings and Precautions (5.6)]
- Serotonin syndrome [see Warnings and Precautions (5.7)]
- Increase in blood pressure [see Warnings and Precautions (5.8)]
- Hypersensitivity reactions [see Contraindications (4), Warnings and Precautions (5.9)]
- Seizures [see Warnings and Precautions (5.10)]

6.1 Clinical Trials Experience

Because clinical trials are conducted under widely varying conditions, adverse reaction rates observed in the clinical trials of a drug cannot be directly compared with rates in the clinical trials of another drug and may not reflect the rates observed in practice.

Table 1 lists adverse reactions that occurred in placebo-controlled clinical trials in patients who took at least 1 dose of study drug. Only treatment-emergent adverse reactions that occurred at a frequency of 2% or more in any group treated with IMITREX tablets and that occurred at a frequency greater than the placebo group are included in Table 1.

Table 1. Adverse Reactions Reported by at Least 2% of Patients Treated with IMITREX Tablets and at a Greater Frequency than Placebo

Adverse Reaction | Percent of Patients Reporting
Adverse Reaction | IMITREX Tablets 25 mg (n = 417) | IMITREX Tablets 50 mg (n = 771) | IMITREX Tablets 100 mg (n = 437) | Placebo (n = 309)
Atypical sensations | 5 | 6 | 6 | 4
Paresthesia (all types) | 3 | 5 | 3 | 2
Sensation warm/cold | 3 | 2 | 3 | 2
Pain and other pressure sensations | 6 | 6 | 8 | 4
Chest - pain/tightness/ pressure and/or heaviness | 1 | 2 | 2 | 1
Neck/throat/jaw - pain/ tightness/pressure | <1 | 2 | 3 | <1
Pain - location specified | 2 | 1 | 1 | 1
Other - pressure/tightness/ heaviness | 1 | 1 | 3 | 2
Neurological
Vertigo | <1 | <1 | 2 | <1
Other
Malaise/fatigue | 2 | 2 | 3 | <1

The incidence of adverse reactions in controlled clinical trials was not affected by gender or age of the patients. There were insufficient data to assess the impact of race on the incidence of adverse reactions.

6.2 Postmarketing Experience

The following adverse reactions have been identified during postapproval use of IMITREX tablets, IMITREX nasal spray, and IMITREX injection. Because these reactions are reported voluntarily from a population of uncertain size, it is not always possible to reliably estimate their frequency or establish a causal relationship to drug exposure. These reactions have been chosen for inclusion due to either their seriousness, frequency of reporting, or causal connection to IMITREX or a combination of these factors.

Cardiovascular

Hypotension, palpitations.

Neurological

Dystonia, tremor.

Reproductive System and Breast Disorders

Breast pain [see Use in Specific Populations (8.2)].

7 DRUG INTERACTIONS

7.1 Ergot-Containing Drugs

Ergot-containing drugs have been reported to cause prolonged vasospastic reactions. Because these effects may be additive, use of ergotamine-containing or ergot-type medications (like dihydroergotamine or methysergide) and IMITREX tablets within 24 hours of each other is contraindicated.

7.2 Monoamine Oxidase-A Inhibitors

MAO‑A inhibitors increase systemic exposure by 7-fold. Therefore, the use of IMITREX tablets in patients receiving MAO‑A inhibitors is contraindicated [see Clinical Pharmacology (12.3)].

7.3 Other 5-HT1 Agonists

Because their vasospastic effects may be additive, coadministration of IMITREX tablets and other 5‑HT1 agonists (e.g., triptans) within 24 hours of each other is contraindicated.

7.4 Selective Serotonin Reuptake Inhibitors/Serotonin Norepinephrine Reuptake Inhibitors and Serotonin Syndrome

Cases of serotonin syndrome have been reported during coadministration of triptans and SSRIs, SNRIs, TCAs, and MAO inhibitors [see Warnings and Precautions (5.7)].

8 USE IN SPECIFIC POPULATIONS

8.1 Pregnancy

Risk Summary

Data from a prospective pregnancy exposure registry and epidemiological studies of pregnant women have not detected an increased frequency of birth defects or a consistent pattern of birth defects among women exposed to sumatriptan compared with the general population (see Data). In developmental toxicity studies in rats and rabbits, oral administration of sumatriptan to pregnant animals was associated with embryolethality, fetal abnormalities, and pup mortality. When administered by the intravenous route to pregnant rabbits, sumatriptan was embryolethal (see Data).

In the U.S. general population, the estimated background risk of major birth defects and of miscarriage in clinically recognized pregnancies is 2% to 4% and 15% to 20%, respectively. The reported rate of major birth defects among deliveries to women with migraine ranged from 2.2% to 2.9% and the reported rate of miscarriage was 17%, which were similar to rates reported in women without migraine.

Clinical Considerations

Disease-Associated Maternal and/or Embryo/Fetal Risk: Several studies have suggested that women with migraine may be at increased risk of preeclampsia during pregnancy.

Data

Human Data: The Sumatriptan/Naratriptan/TREXIMET (sumatriptan and naproxen sodium) Pregnancy Registry, a population-based international prospective study, collected data for sumatriptan from January 1996 to September 2012. The Registry documented outcomes of 626 infants and fetuses exposed to sumatriptan during pregnancy (528 with earliest exposure during the first trimester, 78 during the second trimester, 16 during the third trimester, and 4 unknown). The occurrence of major birth defects (excluding fetal deaths and induced abortions without reported defects and all spontaneous pregnancy losses) during first-trimester exposure to sumatriptan was 4.2% (20/478 [95% CI: 2.6% to 6.5%]) and during any trimester of exposure was 4.2% (24/576 [95% CI: 2.7% to 6.2%]). The sample size in this study had 80% power to detect at least a 1.73- to 1.91-fold increase in the rate of major malformations. The number of exposed pregnancy outcomes accumulated during the registry was insufficient to support definitive conclusions about overall malformation risk or for making comparisons of the frequencies of specific birth defects. Of the 20 infants with reported birth defects after exposure to sumatriptan in the first trimester, 4 infants had ventricular septal defects, including one infant who was exposed to both sumatriptan and naratriptan, and 3 infants had pyloric stenosis. No other birth defect was reported for more than 2 infants in this group.

In a study using data from the Swedish Medical Birth Register, live births to women who reported using triptans or ergots during pregnancy were compared with those of women who did not. Of the 2,257 births with first-trimester exposure to sumatriptan, 107 infants were born with malformations (relative risk 0.99 [95% CI: 0.91 to 1.21]). A study using linked data from the Medical Birth Registry of Norway to the Norwegian Prescription Database compared pregnancy outcomes in women who redeemed prescriptions for triptans during pregnancy, as well as a migraine disease comparison group who redeemed prescriptions for sumatriptan before pregnancy only, compared with a population control group. Of the 415 women who redeemed prescriptions for sumatriptan during the first trimester, 15 had infants with major congenital malformations (OR 1.16 [95% CI: 0.69 to 1.94]) while for the 364 women who redeemed prescriptions for sumatriptan before, but not during, pregnancy, 20 had infants with major congenital malformations (OR 1.83 [95% CI: 1.17 to 2.88]), each compared with the population comparison group. Additional smaller observational studies evaluating use of sumatriptan during pregnancy have not suggested an increased risk of teratogenicity.

Animal Data: Oral administration of sumatriptan to pregnant rats during the period of organogenesis resulted in an increased incidence of fetal blood vessel (cervicothoracic and umbilical) abnormalities. The highest no-effect dose for embryofetal developmental toxicity in rats was 60 mg/kg/day, or approximately 3 times the maximum recommended human dose (MRHD) of 200 mg/day on a mg/m^2 basis. Oral administration of sumatriptan to pregnant rabbits during the period of organogenesis resulted in increased incidences of embryolethality and fetal cervicothoracic vascular and skeletal abnormalities. Intravenous administration of sumatriptan to pregnant rabbits during the period of organogenesis resulted in an increased incidence of embryolethality. The highest oral and intravenous no-effect doses for developmental toxicity in rabbits were 15 (approximately 2 times the MRHD on a mg/m^2 basis) and 0.75 mg/kg/day, respectively.

Oral administration of sumatriptan to rats prior to and throughout gestation resulted in embryofetal toxicity (decreased body weight, decreased ossification, increased incidence of skeletal abnormalities). The highest no-effect dose was 50 mg/kg/day, or approximately 2 times the MRHD on a mg/m^2 basis. In offspring of pregnant rats treated orally with sumatriptan during organogenesis, there was a decrease in pup survival. The highest no-effect dose for this effect was 60 mg/kg/day, or approximately 3 times the MRHD on a mg/m^2 basis. Oral treatment of pregnant rats with sumatriptan during the latter part of gestation and throughout lactation resulted in a decrease in pup survival. The highest no-effect dose for this finding was 100 mg/kg/day, or approximately 5 times the MRHD on a mg/m^2 basis.

8.2 Lactation

Risk Summary

Sumatriptan is excreted in human milk following subcutaneous administration. There is no information regarding sumatriptan concentrations in milk from lactating women following administration of IMITREX tablets. There are no data on the effects of sumatriptan on the breastfed infant or the effects of sumatriptan on milk production. Use of sumatriptan may be associated with transient breast pain [see Adverse Reactions (6.2)].

The developmental and health benefits of breastfeeding should be considered along with the mother’s clinical need for IMITREX tablets and any potential adverse effects on the breastfed infant from sumatriptan or from the underlying maternal condition.

Clinical Considerations

Infant exposure to sumatriptan can be minimized by avoiding breastfeeding for 12 hours after treatment with IMITREX tablets.

8.4 Pediatric Use

Safety and effectiveness in pediatric patients have not been established. IMITREX tablets are not recommended for use in patients younger than 18 years of age.

Two controlled clinical trials evaluated IMITREX nasal spray (5 to 20 mg) in 1,248 adolescent migraineurs aged 12 to 17 years who treated a single attack. The trials did not establish the efficacy of IMITREX nasal spray compared with placebo in the treatment of migraine in adolescents. Adverse reactions observed in these clinical trials were similar in nature to those reported in clinical trials in adults.

Five controlled clinical trials (2 single-attack trials, 3 multiple-attack trials) evaluating oral IMITREX (25 to 100 mg) in pediatric patients aged 12 to 17 years enrolled a total of 701 adolescent migraineurs. These trials did not establish the efficacy of oral IMITREX compared with placebo in the treatment of migraine in adolescents. Adverse reactions observed in these clinical trials were similar in nature to those reported in clinical trials in adults. The frequency of all adverse reactions in these patients appeared to be both dose- and age‑dependent, with younger patients reporting reactions more commonly than older adolescents.

Postmarketing experience documents that serious adverse reactions have occurred in the pediatric population after use of subcutaneous, oral, and/or intranasal IMITREX. These reports include reactions similar in nature to those reported rarely in adults, including stroke, visual loss, and death. A myocardial infarction has been reported in a 14‑year‑old male following the use of oral IMITREX; clinical signs occurred within 1 day of drug administration. Clinical data to determine the frequency of serious adverse reactions in pediatric patients who might receive subcutaneous, oral, or intranasal IMITREX are not presently available.

8.5 Geriatric Use

Clinical trials of IMITREX tablets did not include sufficient numbers of patients aged 65 years and older to determine whether they respond differently from younger patients. Other reported clinical experience has not identified differences in responses between the elderly and younger patients. In general, dose selection for an elderly patient should be cautious, usually starting at the low end of the dosing range, reflecting the greater frequency of decreased hepatic, renal, or cardiac function and of concomitant disease or other drug therapy.

A cardiovascular evaluation is recommended for geriatric patients who have other cardiovascular risk factors (e.g., diabetes, hypertension, smoking, obesity, strong family history of CAD) prior to receiving IMITREX tablets [see Warnings and Precautions (5.1)].

8.6 Hepatic Impairment

The maximum single dose in patients with mild to moderate hepatic impairment should not exceed 50 mg. IMITREX tablets are contraindicated in patients with severe hepatic impairment [see Clinical Pharmacology (12.3)].

10 OVERDOSAGE

Patients in clinical trials (N = 670) received single oral doses of 140 to 300 mg without significant adverse reactions. Volunteers (N = 174) received single oral doses of 140 to 400 mg without serious adverse reactions.

Overdose in animals has been fatal and has been heralded by convulsions, tremor, paralysis, inactivity, ptosis, erythema of the extremities, abnormal respiration, cyanosis, ataxia, mydriasis, salivation, and lacrimation.

The elimination half-life of sumatriptan is approximately 2.5 hours [see Clinical Pharmacology (12.3)], and therefore monitoring of patients after overdose with IMITREX tablets should continue for at least 12 hours or while symptoms or signs persist.

It is unknown what effect hemodialysis or peritoneal dialysis has on the serum concentrations of sumatriptan.

11 DESCRIPTION

IMITREX tablets contain sumatriptan succinate, a selective 5‑HT1B/1D receptor agonist. Sumatriptan succinate is chemically designated as 3-[2-(dimethylamino)ethyl]-N-methyl-indole-5-methanesulfonamide succinate (1:1), and it has the following structure:

The empirical formula is C14H21N3O2S•C4H6O4, representing a molecular weight of 413.5. Sumatriptan succinate is a white to off‑white powder that is readily soluble in water and in saline.

Each IMITREX tablet for oral administration contains 35, 70, or 140 mg of sumatriptan succinate equivalent to 25, 50, or 100 mg of sumatriptan, respectively. Each tablet also contains the inactive ingredients croscarmellose sodium, dibasic calcium phosphate, magnesium stearate, microcrystalline cellulose, and sodium bicarbonate. Each 100-mg tablet also contains hypromellose, iron oxide, titanium dioxide, and triacetin.

12 CLINICAL PHARMACOLOGY

12.1 Mechanism of Action

Sumatriptan binds with high affinity to human cloned 5‑HT1B/1D receptors. Sumatriptan presumably exerts its therapeutic effects in the treatment of migraine headache through agonist effects at the 5‑HT1B/1D receptors on intracranial blood vessels and sensory nerves of the trigeminal system, which result in cranial vessel constriction and inhibition of pro‑inflammatory neuropeptide release.

12.2 Pharmacodynamics

Blood Pressure

Significant elevation in blood pressure, including hypertensive crisis, has been reported in patients with and without a history of hypertension [see Warnings and Precautions (5.8)].

Peripheral (Small) Arteries

In healthy volunteers (N = 18), a trial evaluating the effects of sumatriptan on peripheral (small vessel) arterial reactivity failed to detect a clinically significant increase in peripheral resistance.

Heart Rate

Transient increases in blood pressure observed in some patients in clinical trials carried out during sumatriptan’s development as a treatment for migraine were not accompanied by any clinically significant changes in heart rate.

12.3 Pharmacokinetics

Absorption

The mean maximum concentration following oral dosing with 25 mg is 18 ng/mL (range: 7 to 47 ng/mL) and 51 ng/mL (range: 28 to 100 ng/mL) following oral dosing with 100 mg of sumatriptan. This compares with a Cmax of 5 and 16 ng/mL following dosing with a 5- and 20‑mg intranasal dose, respectively. The mean Cmax following a 6‑mg subcutaneous injection is 71 ng/mL (range: 49 to 110 ng/mL). The bioavailability is approximately 15%, primarily due to presystemic metabolism and partly due to incomplete absorption. The Cmax is similar during a migraine attack and during a migraine‑free period, but the Tmax is slightly later during the attack, approximately 2.5 hours compared with 2.0 hours. When given as a single dose, sumatriptan displays dose proportionality in its extent of absorption (area under the curve [AUC]) over the dose range of 25 to 200 mg, but the Cmax after 100 mg is approximately 25% less than expected (based on the 25‑mg dose).

Effect of Food: A food effect trial involving administration of IMITREX tablets 100 mg to healthy volunteers under fasting conditions and with a high‑fat meal indicated that the Cmax and AUC were increased by 15% and 12%, respectively, when administered in the fed state.

Distribution

Protein binding, determined by equilibrium dialysis over the concentration range of 10 to 1,000 ng/mL is low, approximately 14% to 21%. The effect of sumatriptan on the protein binding of other drugs has not been evaluated. The apparent volume of distribution is 2.7 L/kg.

Metabolism

In vitro studies with human microsomes suggest that sumatriptan is metabolized by MAO, predominantly the A isoenzyme. Most of a radiolabeled dose of sumatriptan excreted in the urine is the major metabolite indole acetic acid (IAA) or the IAA glucuronide, both of which are inactive.

Elimination

The elimination half-life of sumatriptan is approximately 2.5 hours. Radiolabeled ^14C-sumatriptan administered orally is largely renally excreted (about 60%) with about 40% found in the feces. Most of the radiolabeled compound excreted in the urine is the major metabolite, IAA, which is inactive, or the IAA glucuronide. Only 3% of the dose can be recovered as unchanged sumatriptan.

Specific Populations

Age: The pharmacokinetics of sumatriptan in the elderly (mean age: 72 years, 2 males and 4 females) and in subjects with migraine (mean age: 38 years, 25 males and 155 females) were similar to that in healthy male subjects (mean age: 30 years).

Patients with Renal Impairment: The effect of renal impairment on the pharmacokinetics of sumatriptan has not been examined.

Patients with Hepatic Impairment: The liver plays an important role in the presystemic clearance of orally administered sumatriptan. Accordingly, the bioavailability of sumatriptan following oral administration may be markedly increased in patients with liver disease. In one small trial of patients with moderate liver impairment (n = 8) matched for sex, age, and weight with healthy subjects (n = 8), the hepatically-impaired patients had an approximately 70% increase in AUC and Cmax and a Tmax 40 minutes earlier compared with the healthy subjects.

The pharmacokinetics of sumatriptan in patients with severe hepatic impairment has not been studied. The use of IMITREX tablets in this population is contraindicated [see Contraindications (4), Use in Specific Populations (8.6)].

Male and Female Patients: In a trial comparing females to males, no pharmacokinetic differences were observed between genders for AUC, Cmax, Tmax, and half‑life.

Racial Groups: The systemic clearance and Cmax of subcutaneous sumatriptan were similar in black (n = 34) and Caucasian (n = 38) healthy male subjects. Oral sumatriptan has not been evaluated for race differences.

Drug Interaction Studies

Monoamine Oxidase-A Inhibitors: Treatment with MAO-A inhibitors generally leads to an increase of sumatriptan plasma levels [see Contraindications (4), Drug Interactions (7.2)].

Due to gut and hepatic metabolic first-pass effects, the increase of systemic exposure after coadministration of an MAO-A inhibitor with oral sumatriptan is greater than after coadministration of the MAO inhibitors with subcutaneous sumatriptan.

In a trial of 14 healthy females, pretreatment with an MAO-A inhibitor decreased the clearance of subcutaneous sumatriptan, resulting in a 2-fold increase in the area under the sumatriptan plasma concentration-time curve (AUC), corresponding to a 40% increase in elimination half-life.

A small trial evaluating the effect of pretreatment with an MAO-A inhibitor on the bioavailability from a 25-mg oral sumatriptan tablet resulted in an approximately 7-fold increase in systemic exposure.

Alcohol: Alcohol consumed 30 minutes prior to sumatriptan ingestion had no effect on the pharmacokinetics of sumatriptan.

13 NONCLINICAL TOXICOLOGY

13.1 Carcinogenesis, Mutagenesis, Impairment of Fertility

Carcinogenesis

In carcinogenicity studies in mouse and rat, sumatriptan was administered orally for 78 and 104 weeks, respectively, at doses up to 160 mg/kg/day (the high dose in rat was reduced from 360 mg/kg/day during Week 21). There was no evidence in either species of an increase in tumors related to sumatriptan administration. Plasma exposures (AUC) at the highest doses tested were 20 and 8 times that in humans at the maximum recommended human dose (MRHD) of 200 mg/day.

Mutagenesis

Sumatriptan was negative in in vitro (bacterial reverse mutation [Ames], gene cell mutation in Chinese hamster V79/HGPRT, chromosomal aberration in human lymphocytes) and in vivo (rat micronucleus) assays.

Impairment of Fertility

When sumatriptan (5, 50, 500 mg/kg/day) was administered orally to male and female rats prior to and throughout the mating period, there was a treatment-related decrease in fertility secondary to a decrease in mating in animals treated with doses greater than 5 mg/kg/day (less than the MRHD on a mg/m^2 basis). It is not clear whether this finding was due to an effect on males or females or both.

When sumatriptan was administered by subcutaneous injection to male and female rats prior to and throughout the mating period, there was no evidence of impaired fertility at doses up to 60 mg/kg/day.

13.2 Animal Toxicology and/or Pharmacology

Corneal Opacities

Dogs receiving oral sumatriptan developed corneal opacities and defects in the corneal epithelium. Corneal opacities were seen at the lowest dose tested, 2 mg/kg/day, and were present after 1 month of treatment. Defects in the corneal epithelium were noted in a 60‑week study. Earlier examinations for these toxicities were not conducted and no‑effect doses were not established. Plasma exposure at the lowest dose tested was approximately 2 times that in humans at the MRHD.

14 CLINICAL STUDIES

The efficacy of IMITREX tablets in the acute treatment of migraine headaches was demonstrated in 3 randomized, double-blind, placebo-controlled trials. Patients enrolled in these 3 trials were predominately female (87%) and Caucasian (97%), with a mean age of 40 years (range: 18 to 65 years). Patients were instructed to treat a moderate to severe headache. Headache response, defined as a reduction in headache severity from moderate or severe pain to mild or no pain, was assessed up to 4 hours after dosing. Associated symptoms such as nausea, photophobia, and phonophobia were also assessed. Maintenance of response was assessed for up to 24 hours postdose. A second dose of IMITREX tablets or other medication was allowed 4 to 24 hours after the initial treatment for recurrent headache. Acetaminophen was offered to patients in Trials 2 and 3 beginning at 2 hours after initial treatment if the migraine pain had not improved or had worsened. Additional medications were allowed 4 to 24 hours after the initial treatment for recurrent headache or as rescue in all 3 trials. The frequency and time to use of these additional treatments were also determined. In all trials, doses of 25, 50, and 100 mg were compared with placebo in the treatment of migraine attacks. In 1 trial, doses of 25, 50, and 100 mg were also compared with each other.

In all 3 trials, the percentage of patients achieving headache response 2 and 4 hours after treatment was significantly greater among patients receiving IMITREX tablets at all doses compared with those who received placebo. In 1 of the 3 trials, there was a statistically significant greater percentage of patients with headache response at 2 and 4 hours in the 50-mg or 100-mg group when compared with the 25-mg dose groups. There were no statistically significant differences between the 50-mg and 100-mg dose groups in any trial. The results from the 3 controlled clinical trials are summarized in Table 2.

Table 2. Percentage of Patients with Headache Response (Mild or No Headache) 2 and 4 Hours following Treatment

 | IMITREX Tablets; 25 mg |  | IMITREX Tablets; 50 mg |  | IMITREX Tablets; 100 mg |  | Placebo
 | 2 h | 4 h | 2 h | 4 h | 2 h | 4 h | 2 h | 4 h
Trial 1 | 52%a | 67%a | 61%a,b | 78%a,b | 62%a,b | 79%a,b | 27% | 38%
 | (n = 298) |  | (n = 296) |  | (n = 296) |  | (n = 94)
Trial 2 | 52%a | 70%a | 50%a | 68%a | 56%a | 71%a | 26% | 38%
 | (n = 66) |  | (n = 62) |  | (n = 66) |  | (n = 65)
Trial 3 | 52%a | 65%a | 54%a | 72%a | 57%a | 78%a | 17% | 19%
 | (n = 48) |  | (n = 46) |  | (n = 46) |  | (n = 47)

a P<0.05 in comparison with placebo.
b P<0.05 in comparison with 25 mg.

The estimated probability of achieving an initial headache response over the 4 hours following treatment in pooled Trials 1, 2, and 3 is depicted in Figure 1.

Figure 1. Estimated Probability of Achieving Initial Headache Response within 4 Hours of Treatment in Pooled Trials 1, 2, and 3a

aThe figure shows the probability over time of obtaining headache response (no or mild pain) following treatment with oral sumatriptan. The averages displayed are based on pooled data from the 3 clinical controlled trials providing evidence of efficacy. Kaplan‑Meier plot with patients not achieving response and/or taking rescue within 240 minutes censored to 240 minutes.

For patients with migraine-associated nausea, photophobia, and/or phonophobia at baseline, there was a lower incidence of these symptoms at 2 hours (Trial 1) and at 4 hours (Trials 1, 2, and 3) following administration of IMITREX tablets compared with placebo.

As early as 2 hours in Trials 2 and 3, or as early as 4 hours in Trial 1, through 24 hours following the initial dose of study treatment, patients were allowed to use additional treatment for pain relief in the form of a second dose of study treatment or other medication. The estimated probability of patients taking a second dose or other medication for migraine over the 24 hours following the initial dose of study treatment is summarized in Figure 2.

Figure 2. The Estimated Probability of Patients Taking a Second Dose of IMITREX Tablets or Other Medication to Treat Migraine over the 24 Hours following the Initial Dose of Study Treatment in Pooled Trials 1, 2, and 3a

aKaplan‑Meier plot based on data obtained in the 3 clinical controlled trials providing evidence of efficacy with patients not using additional treatments censored to 24 hours. Plot also includes patients who had no response to the initial dose. No remedication was allowed within 2 hours postdose.

There is evidence that doses above 50 mg do not provide a greater effect than 50 mg. There was no evidence to suggest that treatment with IMITREX tablets was associated with an increase in the severity of recurrent headaches. The efficacy of IMITREX tablets was unaffected by presence of aura; duration of headache prior to treatment; gender, age, or weight of the subject; relationship to menses; or concomitant use of common migraine prophylactic drugs (e.g., beta-blockers, calcium channel blockers, tricyclic antidepressants). There were insufficient data to assess the impact of race on efficacy.

16 HOW SUPPLIED/STORAGE AND HANDLING

IMITREX tablets, 25 mg, 50 mg, and 100 mg of sumatriptan (base) as the succinate.

IMITREX tablets, 25 mg, are white, triangular‑shaped, film‑coated tablets debossed with “I” on one side and “25” on the other in blister packs of 9 tablets (NDC 0173-0735-00).

IMITREX tablets, 50 mg, are white, triangular‑shaped, film‑coated tablets debossed with “IMITREX 50” on one side and a chevron shape (^) on the other in blister packs of 9 tablets (NDC 0173-0736-01).

IMITREX tablets, 100 mg, are pink, triangular‑shaped, film‑coated tablets debossed with “IMITREX 100” on one side and a chevron shape (^) on the other in blister packs of 9 tablets (NDC 0173-0737-01).

Store between 2°C and 30°C (36°F and 86°F).

17 PATIENT COUNSELING INFORMATION

Advise the patient to read the FDA-approved patient labeling (Patient Information).

Risk of Myocardial Ischemia and/or Infarction, Prinzmetal’s Angina, Other Vasospasm-Related Events, Arrhythmias, and Cerebrovascular Events

Inform patients that IMITREX tablets may cause serious cardiovascular side effects such as myocardial infarction or stroke. Although serious cardiovascular events can occur without warning symptoms, patients should be alert for the signs and symptoms of chest pain, shortness of breath, irregular heartbeat, significant rise in blood pressure, weakness, and slurring of speech, and should ask for medical advice if any indicative sign or symptoms are observed. Apprise patients of the importance of this follow-up [see Warnings and Precautions (5.1, 5.2, 5.4, 5.5, 5.8)].

Anaphylactic/Anaphylactoid Reactions

Inform patients that anaphylactic/anaphylactoid reactions have occurred in patients receiving IMITREX tablets. Such reactions can be life-threatening or fatal. In general, anaphylactic reactions to drugs are more likely to occur in individuals with a history of sensitivity to multiple allergens [see Contraindications (4), Warnings and Precautions (5.9)].

Concomitant Use with Other Triptans or Ergot Medications

Inform patients that use of IMITREX tablets within 24 hours of another triptan or an ergot-type medication (including dihydroergotamine or methysergide) is contraindicated [see Contraindications (4), Drug Interactions (7.1, 7.3)].

Serotonin Syndrome

Caution patients about the risk of serotonin syndrome with the use of IMITREX tablets or other triptans, particularly during combined use with SSRIs, SNRIs, TCAs, and MAO inhibitors [see Warnings and Precautions (5.7), Drug Interactions (7.4)].

Medication Overuse Headache

Inform patients that use of acute migraine drugs for 10 or more days per month may lead to an exacerbation of headache and encourage patients to record headache frequency and drug use (e.g., by keeping a headache diary) [see Warnings and Precautions (5.6)].

Pregnancy

Advise patients to notify their healthcare provider if they become pregnant during treatment or plan to become pregnant [see Use in Specific Populations (8.1)].

Lactation

Advise breastfeeding women that they may develop transient breast pain when taking IMITREX. Advise breastfeeding women that avoiding breastfeeding for 12 hours after treatment with IMITREX can minimize their infant’s exposure to sumatriptan [see Use in Specific Populations (8.2)].

Ability to Perform Complex Tasks

Treatment with IMITREX tablets may cause somnolence and dizziness; instruct patients to evaluate their ability to perform complex tasks after administration of IMITREX tablets.

IMITREX is a trademark owned by or licensed to the GSK group of companies. The other brand listed is a trademark owned by or licensed to its owner and is not owned by or licensed to the GSK group of companies. The maker of this brand is not affiliated with and does not endorse the GSK group of companies or its products.

Distributed by:

GlaxoSmithKline

Durham, NC 27701

©2025 GSK group of companies or its licensor.

IMT:9PI

PATIENT INFORMATION

IMITREX (IM-i-trex)

(sumatriptan)

tablets

What is the most important information I should know about IMITREX?

IMITREX can cause serious side effects, including:

Heart attack and other heart problems. Heart problems may lead to death.

Stop taking IMITREX and get emergency medical help right away if you have any of the following symptoms of a heart attack:

- discomfort in the center of your chest that lasts for more than a few minutes, or that goes away and comes back
- severe tightness, pain, pressure, or heaviness in your chest, throat, neck, or jaw
- pain or discomfort in your arms, back, neck, jaw, or stomach
- shortness of breath with or without chest discomfort
- breaking out in a cold sweat
- nausea or vomiting
- feeling lightheaded

IMITREX is not for people with risk factors for heart disease unless a heart exam is done and shows no problem. You have a higher risk for heart disease if you:

- have high blood pressure
- have high cholesterol levels
- smoke
- are overweight
- have diabetes
- have a family history of heart disease

What is IMITREX?

IMITREX is a prescription medicine used to treat acute migraine headaches with or without aura in adults.

IMITREX is not used to treat other types of headaches such as hemiplegic (that make you unable to move on one side of your body) or basilar (rare form of migraine with aura) migraines.

IMITREX is not used to prevent or decrease the number of migraine headaches you have.

It is not known if IMITREX is safe and effective to treat cluster headaches.

It is not known if IMITREX is safe and effective in children under 18 years of age.

Do not take IMITREX if you have:

- heart problems or a history of heart problems
- narrowing of blood vessels to your legs, arms, stomach, or kidneys (peripheral vascular disease)
- uncontrolled high blood pressure
- severe liver problems
- hemiplegic migraines or basilar migraines. If you are not sure if you have these types of migraines, ask your healthcare provider.
- had a stroke, transient ischemic attacks (TIAs), or problems with your blood circulation
- taken any of the following medicines in the last 24 hours:

- almotriptan (AXERT)
- frovatriptan (FROVA)
- rizatriptan (MAXALT, MAXALT-MLT)
- ergotamines (CAFERGOT, ERGOMAR, MIGERGOT)

- eletriptan (RELPAX)
- naratriptan (AMERGE)
- sumatriptan and naproxen (TREXIMET)
- dihydroergotamine (D.H.E. 45, MIGRANAL)

Ask your healthcare provider if you are not sure if your medicine is listed above.
2. an allergy to sumatriptan or any of the ingredients in IMITREX. See the end of this leaflet for a complete list of ingredients in IMITREX.

Before you take IMITREX, tell your healthcare provider about all of your medical conditions, including if you:

- have high blood pressure.
- have high cholesterol.
- have diabetes.
- smoke.
- are overweight.
- have heart problems or family history of heart problems or stroke.
- have kidney problems.
- have liver problems.
- have had epilepsy or seizures.
- are not using effective birth control.
- are pregnant or plan to become pregnant. It is not known if IMITREX can harm your unborn baby.
- are breastfeeding or plan to breastfeed. IMITREX passes into your breast milk. It is not known if this can harm your baby. Talk with your healthcare provider about the best way to feed your baby if you take IMITREX.

Tell your healthcare provider about all the medicines you take, including prescription and over-the-counter medicines, vitamins, and herbal supplements.

IMITREX and certain other medicines can affect each other, causing serious side effects.

Especially tell your healthcare provider if you take antidepressant medicines called:

- selective serotonin reuptake inhibitors (SSRIs)
- serotonin norepinephrine reuptake inhibitors (SNRIs)
- tricyclic antidepressants (TCAs)
- monoamine oxidase inhibitors (MAOIs)

Ask your healthcare provider or pharmacist for a list of these medicines if you are not sure.

Know the medicines you take. Keep a list of them to show your healthcare provider or pharmacist when you get a new medicine.

How should I take IMITREX?

- Certain people should take their first dose of IMITREX in their healthcare provider’s office or in another medical setting. Ask your healthcare provider if you should take your first dose in a medical setting.
- Take IMITREX exactly as your healthcare provider tells you to take it.
- Your healthcare provider may change your dose. Do not change your dose without first talking to your healthcare provider.
- Take IMITREX tablets whole with water or other liquids.
- If you do not get any relief after your first tablet, do not take a second tablet without first talking with your healthcare provider.
- If your headache comes back or you only get some relief from your headache, you can take a second tablet 2 hours after the first tablet.
- Do not take more than 200 mg of IMITREX tablets in a 24‑hour period.
- If you take too much IMITREX, call your healthcare provider or go to the nearest hospital emergency room right away.
- You should write down when you have headaches and when you take IMITREX so you can talk with your healthcare provider about how IMITREX is working for you.

What should I avoid while taking IMITREX?

IMITREX can cause dizziness, weakness, or drowsiness. If you have these symptoms, do not drive a car, use machinery, or do anything where you need to be alert.

What are the possible side effects of IMITREX?

IMITREX may cause serious side effects. See “What is the most important information I should know about IMITREX?”

These serious side effects include:

- changes in color or sensation in your fingers and toes (Raynaud’s syndrome)
- stomach and intestinal problems (gastrointestinal and colonic ischemic events). Symptoms of gastrointestinal and colonic ischemic events include:

- sudden or severe stomach pain
- stomach pain after meals
- weight loss
- fever

- nausea or vomiting
- constipation or diarrhea
- bloody diarrhea

- problems with blood circulation to your legs and feet (peripheral vascular ischemia). Symptoms of peripheral vascular ischemia include:
  - cramping and pain in your legs or hips
  - feeling of heaviness or tightness in your leg muscles
  - burning or aching pain in your feet or toes while resting
  - numbness, tingling, or weakness in your legs
  - cold feeling or color changes in 1 or both legs or feet
- medication overuse headaches. Some people who use too many IMITREX tablets may have worse headaches (medication overuse headache). If your headaches get worse, your healthcare provider may decide to stop your treatment with IMITREX.
- serotonin syndrome. Serotonin syndrome is a rare but serious problem that can happen in people using IMITREX, especially if IMITREX is used with anti-depressant medicines called SSRIs or SNRIs.
Call your healthcare provider right away if you have any of the following symptoms of serotonin syndrome:
  1. mental changes such as seeing things that are not there (hallucinations), agitation, or coma
  2. fast heartbeat
  3. changes in blood pressure
  4. high body temperature
  5. tight muscles
  6. trouble walking
- hives (itchy bumps); swelling of your tongue, mouth, or throat.
- seizures. Seizures have happened in people taking IMITREX who have never had seizures before. Talk with your healthcare provider about your chance of having seizures while you take IMITREX.

The most common side effects of IMITREX tablets include:

- tingling or numbness in your fingers or toes
- warm or cold feeling
- feeling weak, drowsy, or tired
- pain, discomfort, or stiffness in your neck, throat, jaw, or chest
- dizziness

Tell your healthcare provider if you have any side effect that bothers you or that does not go away.

These are not all the possible side effects of IMITREX. Call your doctor for medical advice about side effects. You may report side effects to FDA at 1-800-FDA-1088.

How should I store IMITREX Tablets?

Store IMITREX between 36°F to 86°F (2°C to 30°C).

Keep IMITREX and all medicines out of the reach of children.

General information about the safe and effective use of IMITREX.

Medicines are sometimes prescribed for purposes other than those listed in Patient Information leaflets. Do not use IMITREX for a condition for which it was not prescribed. Do not give IMITREX to other people, even if they have the same symptoms you have. It may harm them.

This Patient Information leaflet summarizes the most important information about IMITREX. If you would like more information, talk with your healthcare provider. You can ask your healthcare provider or pharmacist for information about IMITREX that is written for healthcare professionals.

For more information, call 1-888-825-5249.

What are the ingredients in IMITREX Tablets?

Active ingredient: sumatriptan succinate

Inactive ingredients: croscarmellose sodium, dibasic calcium phosphate, magnesium stearate, microcrystalline cellulose, and sodium bicarbonate

100‑mg tablets also contain hypromellose, iron oxide, titanium dioxide, and triacetin.

IMITREX and AMERGE are owned by or licensed to the GSK group of companies. The other brands listed are trademarks owned by or licensed to their respective owners and are not owned by or licensed to the GSK group of companies. The makers of these brands are not affiliated with and do not endorse the GSK group of companies or its products.

Distributed by:

GlaxoSmithKline

Durham, NC 27701

©2024 GSK group of companies or its licensor.

IMT:8PIL

This Patient Information has been approved by the U.S. Food and Drug Administration. Revised: February 2024

PACKAGE LABEL

PRINCIPAL DISPLAY PANEL

NDC 0173-0735-00

IMITREX

(SUMATRIPTAN)

TABLETS

25 mg

GSK

Rx only

Each tablet contains 35 mg sumatriptan succinate equivalent to 25 mg of sumatriptan.

9 Tablets

Do not use if package is torn or broken or if you receive fewer tablets than your doctor prescribed.

Made in India

©2024 GSK group of companies or its licensor.

546544-03 Rev. 11/24

PACKAGE LABEL

PRINCIPAL DISPLAY PANEL

NDC 0173-0736-01

IMITREX

(SUMATRIPTAN)

TABLETS

50 mg

GSK

Rx only

Each tablet contains 70 mg sumatriptan succinate equivalent to 50 mg of sumatriptan.

9 Tablets

Do not use if package is torn or broken or if you receive fewer tablets than your doctor prescribed.

Made in India

©2024 GSK group of companies or its licensor.

546545-03 Rev.11/24

PACKAGE LABEL

PRINCIPAL DISPLAY PANEL

NDC 0173-0737-01

IMITREX

(SUMATRIPTAN)

TABLETS

100 mg

GSK

Rx only

Each tablet contains 140 mg sumatriptan succinate equivalent to 100 mg of sumatriptan.

9 Tablets

Do not use if package is torn or broken or if you receive fewer tablets than your doctor prescribed.

Made in India

©2024 GSK group of companies or its licensor.

546546-03 Rev. 11/24